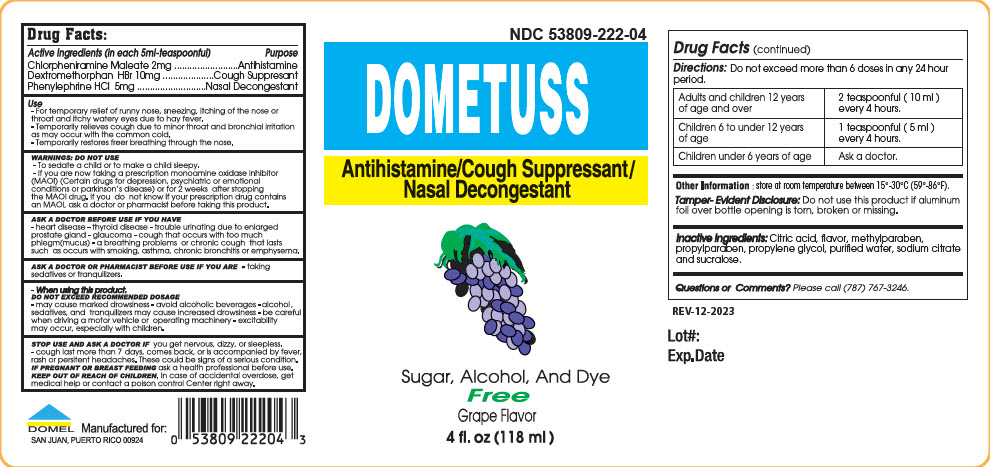 DRUG LABEL: DOMETUSS
NDC: 53809-222 | Form: LIQUID
Manufacturer: Domel Laboratories
Category: otc | Type: HUMAN OTC DRUG LABEL
Date: 20250916

ACTIVE INGREDIENTS: CHLORPHENIRAMINE MALEATE 2 mg/5 mL; DEXTROMETHORPHAN HYDROBROMIDE 10 mg/5 mL; PHENYLEPHRINE HYDROCHLORIDE 5 mg/5 mL
INACTIVE INGREDIENTS: CITRIC ACID MONOHYDRATE; METHYLPARABEN; PROPYLPARABEN; PROPYLENE GLYCOL; WATER; SODIUM CITRATE, UNSPECIFIED FORM; SUCRALOSE

DOMETUSS

Drug Facts:

ACTIVE INGREDIENT

Active Ingredients (in each 5ml-teaspoonful) | Purpose
Chlorpheniramine Maleate 2mg | Antihistamine
Dextromethorphan HBr 10mg | Cough Suppresant
Phenylephrine HCl 5mg | Nasal Decongestant

Use

- For temporary relief of runny nose, sneezing, itching of the nose or throat and itchy watery eyes due to hay fever.
- Temporarily relieves cough due to minor throat and bronchial irritation as may occur with the common cold.
- Temporarily restores freer breathing through the nose.

WARNINGS

DO NOT USE

- To sedate a child or to make a child sleepy.
- If you are now taking a prescription monoamine oxidase inhibitor (MAOI) (Certain drugs for depression, psychiatric or emotional conditions or parkinson's disease) or for 2 weeks after stopping the MAOI drug. If you do not know if your prescription drug contains an MAOI, ask a doctor or pharmacist before taking this product.

ASK A DOCTOR BEFORE USE IF YOU HAVE

- heart disease
- thyroid disease
- trouble urinating due to enlarged prostate gland
- glaucoma
- cough that occurs with too much phlegm(mucus)
- a breathing problems or chronic cough that lasts such as occurs with smoking, asthma, chronic bronchitis or emphysema.

ASK A DOCTOR OR PHARMACIST BEFORE USE IF YOU ARE

- taking sedatives or tranquilizers.

- When using this product.
  DO NOT EXCEED RECOMMENDED DOSAGE
- may cause marked drowsiness
- avoid alcoholic beverages
- alcohol, sedatives, and tranquilizers may cause increased drowsiness
- be careful when driving a motor vehicle or operating machinery
- excitability may occur, especially with children.

STOP USE AND ASK A DOCTOR IF you get nervous, dizzy, or sleepless.

- cough last more than 7 days, comes back, or is accompanied by fever, rash or persitent headaches. These could be signs of a serious condition.

PREGNANCY OR BREAST FEEDING

IF PREGNANT OR BREAST FEEDING ask a health professional before use.

KEEP OUT OF REACH OF CHILDREN. In case of accidental overdose, get medical help or contact a poison control Center right away.

Directions

Do not exceed more than 6 doses in any 24 hour period.

Adults and children 12 years of age and over | 2 teaspoonful (10 ml) every 4 hours.
Children 6 to under 12 years of age | 1 teaspoonful (5 ml) every 4 hours.
Children under 6 years of age | Ask a doctor.

Other Information

store at room temperature between 15°-30°C (59°-86°F).

Tamper-Evident Disclosure

Do not use this product if aluminum foil over bottle opening is torn, broken or missing.

Inactive ingredients

Citric acid, flavor, methylparaben, propylparaben, propylene glycol, purified water, sodium citrate and sucralose.

Questions or comments?

Please call (787) 767-3246.

PRINCIPAL DISPLAY PANEL - 118 mL Bottle Label

NDC 53809-222-04

DOMETUSS

Antihistamine/Cough Suppressant/
Nasal Decongestant

Sugar, Alcohol, And Dye
Free
Grape Flavor

4 fl. oz (118 ml)